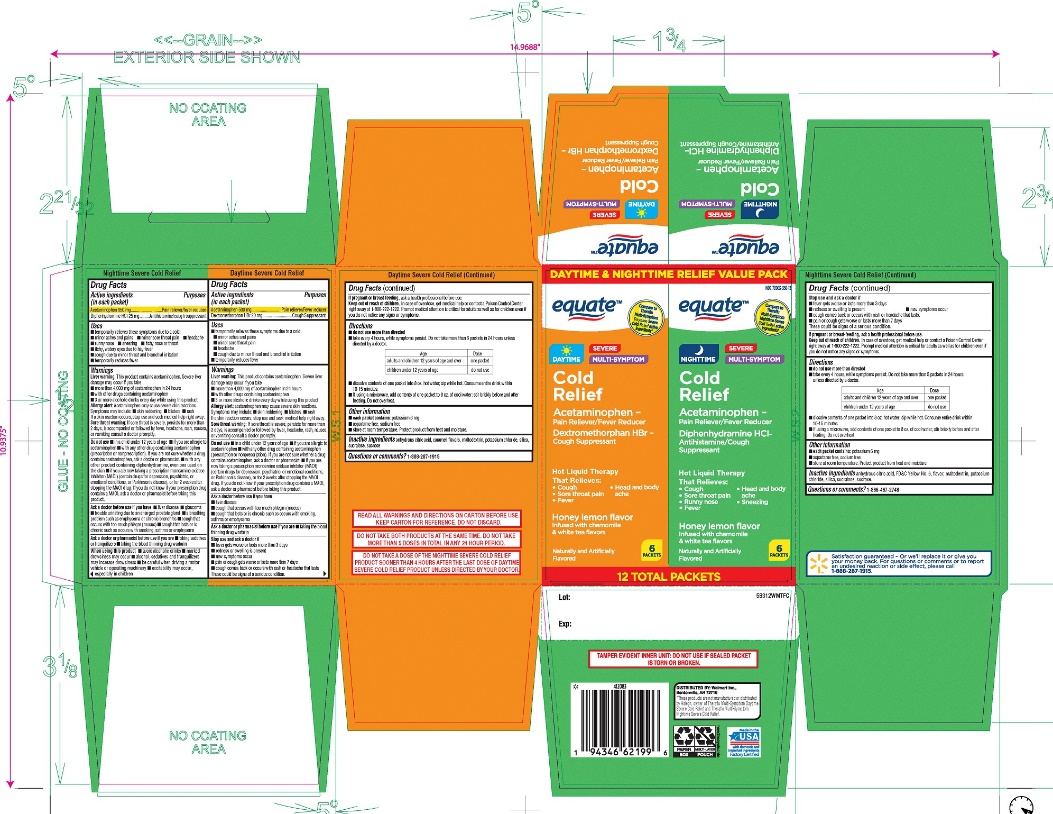 DRUG LABEL: WALMART
NDC: 79903-350 | Form: KIT | Route: ORAL
Manufacturer: WAL-MART STORES INC
Category: otc | Type: HUMAN OTC DRUG LABEL
Date: 20260219

ACTIVE INGREDIENTS: ACETAMINOPHEN 500 mg/1 1; DEXTROMETHORPHAN HYDROBROMIDE 20 mg/1 1; ACETAMINOPHEN 650 mg/1 1; DIPHENHYDRAMINE HYDROCHLORIDE 25 mg/1 1
INACTIVE INGREDIENTS: ANHYDROUS CITRIC ACID; CARAMEL; MALTODEXTRIN; POTASSIUM CHLORIDE; SILICON DIOXIDE; SUCRALOSE; SUCROSE; ANHYDROUS CITRIC ACID; FD&C YELLOW NO. 6; MALTODEXTRIN; POTASSIUM CHLORIDE; SILICON DIOXIDE; SUCRALOSE; SUCROSE

equate Daytime & Nighttime relief Value Pack

Active ingredients (in each packet) – Daytime Severe Cold Relief

Acetaminophen 500 mg

Dextromethorphan hydrobromide 20 mg

Active ingredients (in each packet) - Nighttime Severe Cold Relief

Acetaminophen 650 mg

Diphenhydramine hydrochloride 25 mg

Purpose - Daytime Severe Cold Relief

Pain reliever/fever reducer

Cough Suppressant

Purpose - Nighttime Severe Cold Relief

Pain reliever/fever reducer

Antihistamine/Cough suppressant

Uses - Daytime Severe Cold Relief

- temporarily relieves these symptoms due to a cold:
- minor aches and pains
- minor sore throat pain
- headache
- cough due to minor throat and bronchial irritation
- temporarily reduces fever

Uses - Nighttime Severe Cold Relief

- temporarily relieves these symptoms due to a cold:
- minor aches and pains
- minor sore throat pain
- headache
- runny nose
- sneezing
- itchy nose or throat
- itchy, watery eyes due to hay fever
- cough due to minor throat and bronchial irritation
- temporarily reduces fever

Warnings – Daytime Severe Cold Relief /Nighttime Severe Cold Relief

Liver warning: This product contains acetaminophen. Severe liver damage may occur if you take

- more than 4,000 mg of acetaminophen in 24 hours
- with other drugs containing acetaminophen
- 3 or more alcoholic drinks every day while using this product

Allergy alert: Acetaminophen may cause severe skin reactions. Symptoms may include:

- skin reddening
- blisters
- rash

If a skin reaction occurs, stop use and seek medical help right away

Sore throat warning: If sore throat is severe, persists for more than 2 days, is accompanied or followed by fever, headache, rash, nausea, or vomiting, consult a doctor promptly.

Do not use - Daytime Severe Cold Relief

- in a child under 12 years of age
- if you are allergic to acetaminophen
- with any other drug containing acetaminophen (prescription or nonprescription). If you are not sure whether a drug contains acetaminophen, ask a doctor or a pharmacist.
- if you are now taking a prescription monoamine oxidase inhibitor (MAOI) (certain drugs for depression, psychiatric, or emotional conditions, or Parkinson's disease), or for 2 weeks after stopping the MAOI drug. If you do not know if your prescription drug contains an MAOI, ask a doctor or pharmacist before taking this product.

Do not use - Nighttime Severe Cold Relief

- in a child under 12 years of age
- if you are allergic to acetaminophen
- with any other drug containing acetaminophen (prescription or nonprescription). If you are not sure whether a drug contains acetaminophen, ask a doctor or a pharmacist.
- with any other product containing diphenhydramine, even one used on skin
- if you are now taking a prescription monoamine oxidase inhibitor (MAOI) (certain drugs for depression, psychiatric, or emotional conditions, or Parkinson’s disease), or for 2 weeks after stopping the MAOI drug. If you do not know if your prescription drug contains an MAOI, ask a doctor or pharmacist before taking this product.

Ask a doctor before use if you have - Daytime Severe Cold Relief

- liver disease
- cough that occurs with too much phlegm (mucus)
- cough that lasts or is chronic such as occurs with smoking, asthma, or emphysema

Ask a doctor before use if you have - Nighttime Severe Cold Relief

- liver disease
- glaucoma
- trouble urinating due to an enlarged prostate gland
- a breathing problem such as emphysema or chronic bronchitis
- cough that occurs with too much phlegm (mucus)
- cough that lasts or is chronic such as occurs with smoking, asthma, or emphysema

Ask a doctor or pharmacist before use if you are - Daytime Severe Cold Relief

- taking the blood thinning drug warfarin

Ask a doctor or pharmacist before use if you are - Nighttime Severe Cold Relief

- taking sedatives or tranquilizers
- taking the blood thinning drug warfarin

When using this product - Daytime Severe Cold Relief

do not exceed recommended dosage

When using this product - Nighttime Severe Cold Relief

- avoid alcoholic drinks
- marked drowsiness may occur
- alcohol, sedatives, and tranquilizers may increase drowsiness
- be careful when driving a motor vehicle or operating machinery
- excitability may occur, especially in children

Stop use and ask a doctor if – Daytime Severe Cold Relief /Nighttime Severe Cold and Cough

fever gets worse or lasts more than 3 days

- redness or swelling is present
- new symptoms occur
- pain, or cough gets worse or lasts more than 7 days
- cough comes back or occurs with rash or headache that lasts. These could be signs of a serious condition.

If pregnant or breast-feeding,

ask a health professional before use.

Keep out of reach of children.

In case of overdose, get medical help or contact a Poison Control Center right away (1-800-222-1222). Prompt medical attention is critical for adults as well as for children even if you do not notice any signs or symptoms.

Directions – Daytime Severe Cold Relief

- do not use more than directed
- take every 4 hours, while symptoms persist. Do not take more than 6 packets in 24 hours unless directed by a doctor

Age | Dose
Adults and children 12 years of age and over | One packet
Children under 12 years of age | Do not use

- dissolve contents of one packet into 8 oz. hot water: sip while hot. Consume entire drink within 10 - 15 minutes.
- if using a microwave, add contents of one packet to 8 oz. of cool water: stir briskly before and after heating, Do not overheat

Directions Nighttime Severe Cold Relief

- do not use more than directed
- take every 4 hours while symptoms persist, Do not take more than 5 packets in 24 hours unless directed by a doctor

Age | Dose
Adults and Children 12 years of age and over | One packet
Children under 12 years of age | do not use

- dissolve contents of one packet into 8 oz. hot water: sip while hot. Consume entire drink within 10 - 15 minutes.
- if using a microwave, add contents of one packet to 8 oz. of cool water: stir briskly before and after heating, Do not overheat.

Other information - Daytime Severe Cold Relief

- each packet contains:potassium 6 mg
- Aspartame free, sodium free
- store at room temperature. Protect from excessive heat and moisture.

Other information - Nighttime Severe Cold Relief

- each packet contains: potassium 6 mg
- Aspartame free, sodium free
- store at room temperature. Protect from excessive heat and moisture

Inactive ingredients - Daytime Severe Cold Relief

anhydrous citric acid, caramel, flavors, maltodextrin, potassium chloride, silica, sucralose, sucrose

Inactive ingredients - Nighttime Severe Cold Relief

anhydrous citric acid, F D & C yellow #6 , flavors, maltodextrin, potassium chloride, silica ,sucralose, sucrose,

Questions or comments?

1-866-467-2748

Package/Label Principal Display Panel

NDC# 49035-948-12

DAYTIME & NIGHTTIME RELIEF VALUE PACK

Compare to Theraflu® Multi Symptom Severe Cold Relief active ingredients* Nighttime Severe Cold Relief active ingredients*

NDC 79903-350-12

DAYTIME SEVERE MULTI- SYMPTOM

COLD RELIEF

Acetaminophen - Pain Reliever/ Fever Reducer

Dextromethorphan HBr - Cough Suppressant

Hot Liquid Therapy That Relieves

- Cough
- Head & Body
- Sore throat pain
- ache
- Fever

Honey Lemon Flavor

Infused with chamomile and white tea flavors

Naturally and Artificially Flavored

6 PACKETS

NIGHTTIME SEVERE MULTI-SYMPTOM

COLD Relief

Acetaminophen - Pain Reliever/ Fever Reducer

Dextromethorphan HBr - Cough Suppressant

Hot Liquid Therapy That Relieves

- Cough
- Head & Body
- Sore throat pain
- Ache
- Runny nose
- Sneezing
- Fever

Honey lemon flavor

Infused with chamomile & white tea flavors

6 PACKETS

12 TOTAL PACKETS

READ ALL WARNINGS AND DIRECTIONS ON CARTON BEFORE USE .KEEP CARTON FOR REFERENCE, DO NOT DISCARD.

DO NOT TAKE BOTH PRODUCTS AT THE SAME TIME OR TAKE MORE THAN 5 DOSES IN TOTAL IN ANY 24 –HOUR PERIOD.

DO NOT TAKE A DOSE OF THE NIGHTTIME PRODUCT SOONER THAN 4 HOURS AFTER THE LAST DOSE OF DAYTIME PRODUCT UNLESS DIRECTED BY DOCTOR.

*These Products are not manufactured or distributed by Haleon, owner of Theraflu® Multi-Symptom Daytime Severe Cold & Theraflu® Multi-Symptom Nighttime Severe Cold Relief.

Distributed By: Wal-Mart Stores, Inc. Bentonville, AR 72716

© Wal-Mart Stores, Inc.

Satisfaction guaranteed – or we’ll replace it or give you your money back. For questions or comments or to report an undesired reaction or side effect, please call 1-888-287-1915

TAMPER EVIDENT INNER UNIT: DO NOT USE IF SEALED PACKET IS TORN OR BROKEN